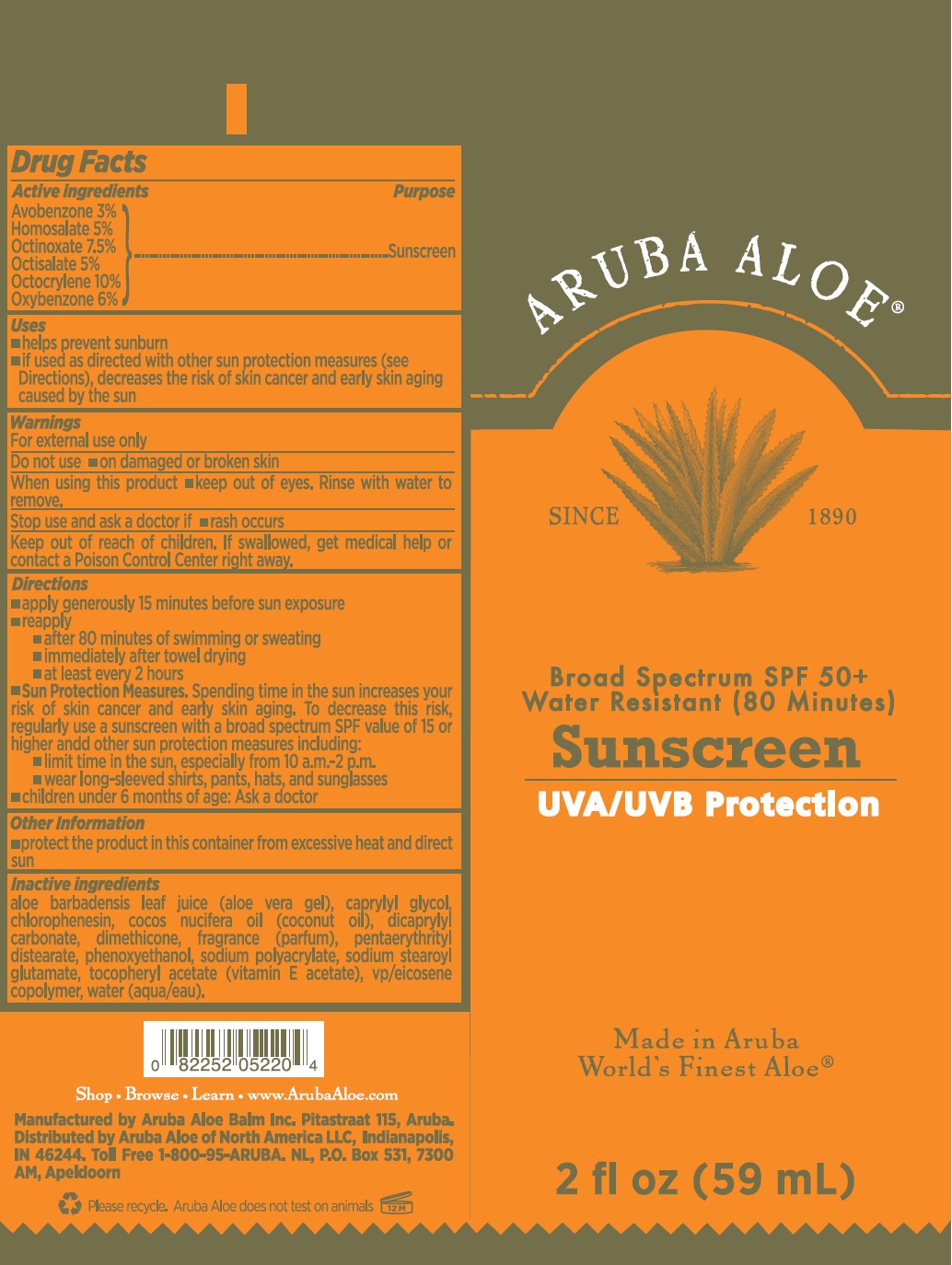 DRUG LABEL: Sunscreen SPF 50 Plus Broad Spectrum UVA UVB protection
NDC: 53675-165 | Form: CREAM
Manufacturer: Aruba Aloe Balm NV
Category: otc | Type: HUMAN OTC DRUG LABEL
Date: 20260211

ACTIVE INGREDIENTS: AVOBENZONE 30 mg/1 mL; HOMOSALATE 50 mg/1 mL; OCTINOXATE 75 mg/1 mL; OCTISALATE 50 mg/1 mL; OCTOCRYLENE 100 mg/1 mL; OXYBENZONE 60 mg/1 mL
INACTIVE INGREDIENTS: ALOE VERA LEAF; CAPRYLYL GLYCOL; CHLORPHENESIN; COCONUT OIL; DICAPRYLYL CARBONATE; DIMETHICONE; .ALPHA.-TOCOPHEROL ACETATE; WATER

Sunscreen SPF 50 Plus Broad Spectrum UVA UVB protection

Active ingredients

Avobenzone 3%

Homosalate 5%

Octinoxate 7.5%

Octisalate 5%

Octocrylene 10%

Oxybenzone 6%

Purpose

Sunscreen

Uses

• helps prevent sunburn

• if used as directed with other sun protection measures (see Directions), decreases the risk of skin cancer and early skin aging caused by the sun

Warnings

For external use only

Do not use

• on damaged or broken skin

When using this product

• keep out of eyes. Rinse with water to remove.

Stop use and ask a doctor if

• rash occurs

Keep out of reach of children.

If swallowed, get medical help or contact a Poison Control Center right away.

Directions

- apply generously 15 minutes before sun exposure
- reapply
- after 80 minutes of swimming of sweating
- immediately after towel drying
- at least every 2 hours
- Spending time in the sun increases your risk of skin cancer and early skin aging. To decrease this risk, regularly use a sunscreen with a broad spectrum SPF value of 15 or higher andd other sun protection measures including: Sun Protection Measures.
- limit time in the sun, especially from 10 a.m.-2p.m.
- wear long-sleeved shirts, pants, hats, and sunglasses
- children under 6 months of age: Ask a doctor

Other Information

• protect the product in this container from excessive heat and direct sun

Inactive ingredients

aloe barbadensis leaf juice (aloe vera gel), caprylyl glycol, chlorophenesin, cocos nucifera oil (coconut oil), dicaprylyl carbonate, dimethicone, fragrance (parfum), pentaerythrityl glutamate, tocopheryl acetate (vitamin E acetate), vp/eicosene copolymer, water (aqua/eau).